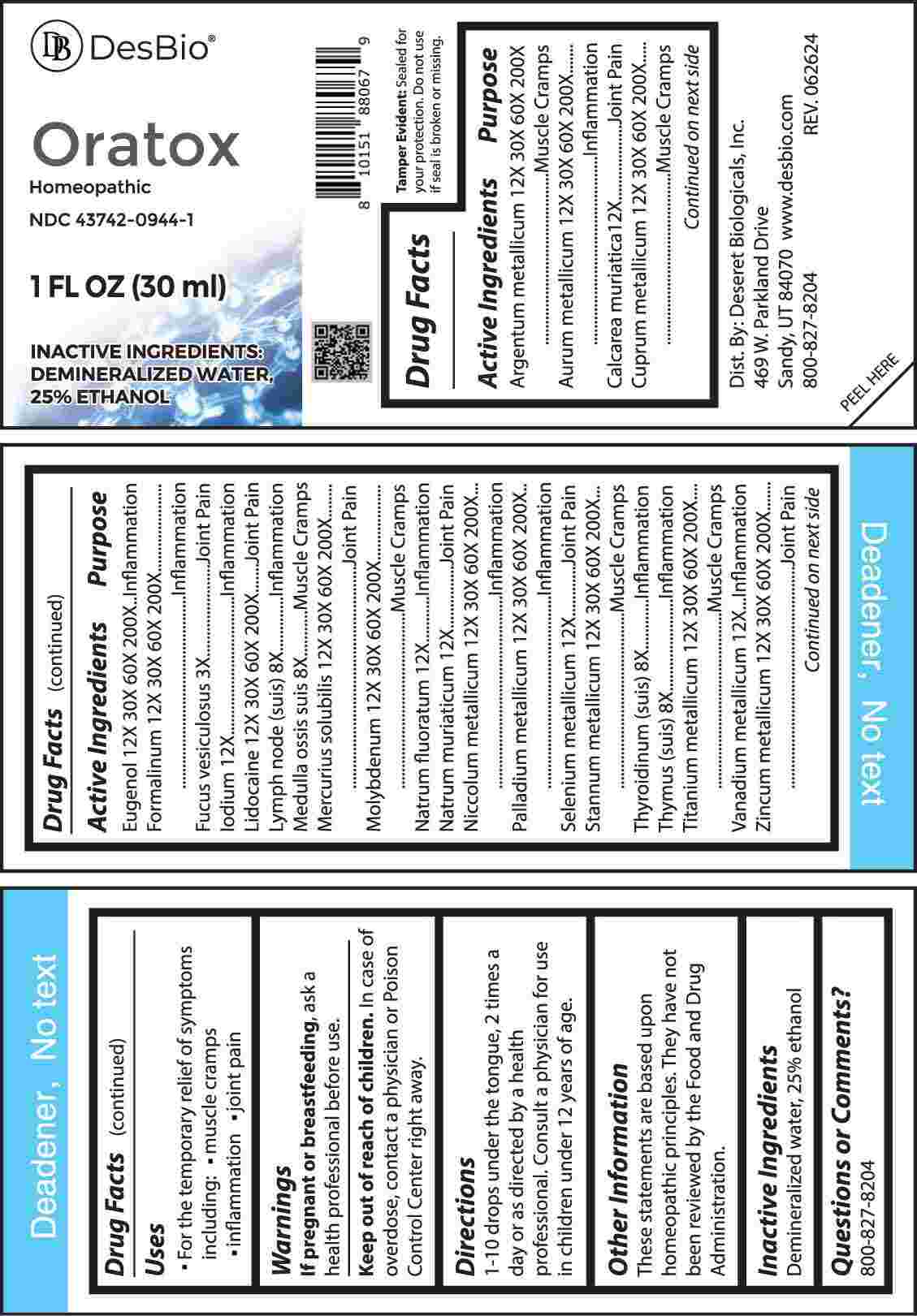 DRUG LABEL: Oratox
NDC: 43742-0944 | Form: LIQUID
Manufacturer: Deseret Biologicals, Inc.
Category: homeopathic | Type: HUMAN OTC DRUG LABEL
Date: 20241023

ACTIVE INGREDIENTS: FUCUS VESICULOSUS 3 [hp_X]/1 mL; SUS SCROFA LYMPH 8 [hp_X]/1 mL; SUS SCROFA BONE MARROW 8 [hp_X]/1 mL; SUS SCROFA THYMUS 8 [hp_X]/1 mL; THYROID 8 [hp_X]/1 mL; CALCIUM CHLORIDE 12 [hp_X]/1 mL; IODINE 12 [hp_X]/1 mL; SODIUM FLUORIDE 12 [hp_X]/1 mL; SODIUM CHLORIDE 12 [hp_X]/1 mL; SELENIUM 12 [hp_X]/1 mL; VANADIUM 12 [hp_X]/1 mL; SILVER 12 [hp_X]/1 mL; GOLD 12 [hp_X]/1 mL; COPPER 12 [hp_X]/1 mL; EUGENOL 12 [hp_X]/1 mL; FORMALDEHYDE 12 [hp_X]/1 mL; LIDOCAINE 12 [hp_X]/1 mL; MERCURIUS SOLUBILIS 12 [hp_X]/1 mL; MOLYBDENUM 12 [hp_X]/1 mL; NICKEL 12 [hp_X]/1 mL; PALLADIUM 12 [hp_X]/1 mL; TIN 12 [hp_X]/1 mL; TITANIUM 12 [hp_X]/1 mL; ZINC 12 [hp_X]/1 mL
INACTIVE INGREDIENTS: WATER; ALCOHOL

DRUG FACTS:

ACTIVE INGREDIENTS:

Argentum Metallicum 12X, 30X, 60X, 200X, Aurum Metallicum 12X, 30X, 60X, 200X, Calcarea Muriatica 12X, Cuprum Metallicum 12X, 30X, 60X, 200X, Eugenol 12X, 30X, 60X, 200X, Formalinum 12X, 30X, 60X, 200X, Fucus Vesiculosus 3X, Iodium 12X, Lidocaine 12X, 30X, 60X, 200X, Lymph Node (Suis) 8X, Medulla Ossis Suis 8X, Mercurius Solubilis 12X, 30X, 60X, 200X, Molybdenum 12X, 30X, 60X, 200X, Natrum Fluoratum 12X, Natrum Muriaticum 12X, Niccolum Metallicum 12X, 30X, 60X, 200X, Palladium Metallicum 12X, 30X, 60X, 200X, Selenium Metallicum 12X, Stannum Metallicum 12X, 30X, 60X, 200X, Thyroidinum (Suis) 8X, Thymus (Suis) 8X, Titanium Metallicum 12X, 30X, 60X, 200X, Vanadium Metallicum 12X, Zincum Metallicum 12X, 30X, 60X, 200X.

PURPOSE:

Argentum Metallicum – Muscle Cramps, Aurum Metallicum - Inflammation, Calcarea Muriatica – Joint Pain, Cuprum Metallicum – Muscle Cramps, Eugenol - Inflammation, Formalinum - Inflammation, Fucus Vesiculosus – Joint Pain, Iodium - Inflammation, Lidocaine – Joint Pain, Lymph Node (Suis) - Inflammation, Medulla Ossis Suis – Muscle Cramps, Mercurius Solubilis – Joint Pain, Molybdenum – Muscle Cramps, Natrum Fluoratum - Inflammation, Natrum Muriaticum – Joint Pain, Niccolum Metallicum - Inflammation, Palladium Metallicum - Inflammation, Selenium Metallicum – Joint Pain, Stannum Metallicum – Muscle Cramps, Thyroidinum (Suis) - Inflammation, Thymus (Suis) - Inflammation, Titanium Metallicum – Muscle Cramps, Vanadium Metallicum - Inflammation, Zincum Metallicum – Joint Pain

USES:

• For the temporary relief of symptoms including:

• muscle cramps • inflammation • joint pain

These statements are based upon homeopathic principles. They have not been reviewed by the Food and Drug Administration.

WARNINGS:

If pregnant or breast-feeding, ask a health professional before use.

Keep out of reach of children. In case of overdose, contact a physician or Poison Control Center right away.

Tamper Evident: Sealed for your protection. Do not use if seal is broken or missing.

KEEP OUT OF REACH OF CHILDREN:

In case of overdose, contact a physician or Poison Control Center right away.

DIRECTIONS:

1-10 drops under the tongue, 2 times a day or as directed by a health professional. Consult a physician for use in children under 12 years of age.

INACTIVE INGREDIENTS:

Demineralized water, 25% ethanol

QUESTIONS:

Dist. By: Deseret Biologicals, Inc.
469 W. Parkland Drive
Sandy, UT 84070

www.desbio.com

800-827-8204

PACKAGE LABEL DISPLAY:

DesBio

Oratox

Homeopathic

NDC 43742-0944-1

1 FL OZ (30 ml)